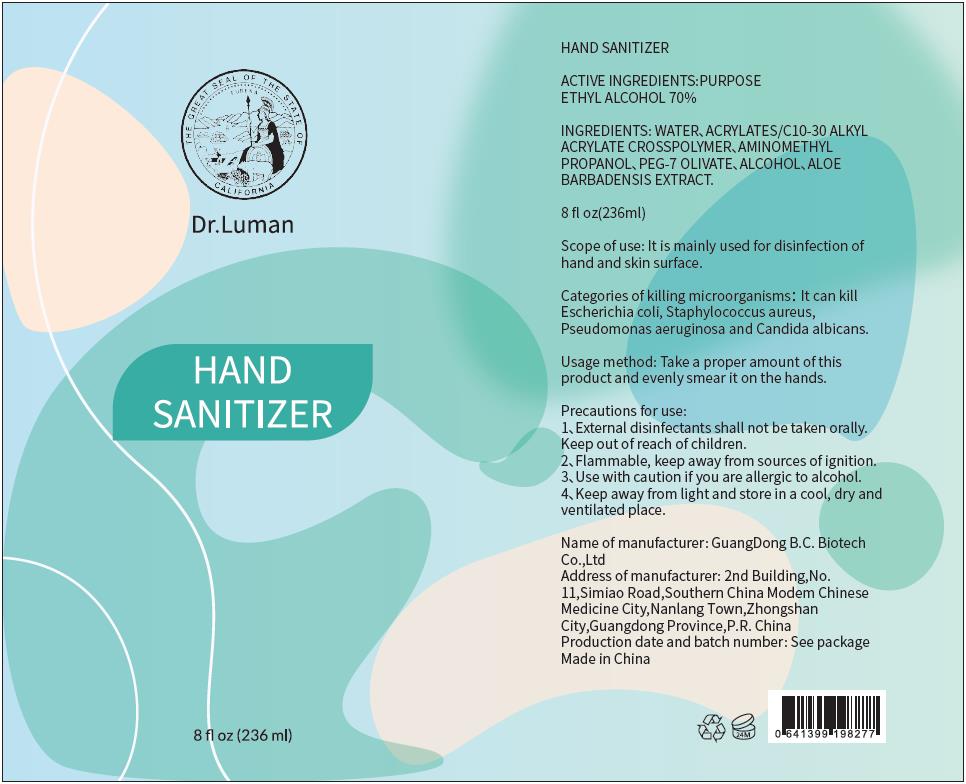 DRUG LABEL: HAND SANITIZER
NDC: 74738-1103 | Form: GEL
Manufacturer: GuangDong B.C. Biotech Co., Ltd.
Category: otc | Type: HUMAN OTC DRUG LABEL
Date: 20200421

ACTIVE INGREDIENTS: ALCOHOL 165.2 mL/236 mL
INACTIVE INGREDIENTS: PEG-7 STEARATE 4.72 mL/236 mL; CARBOMER INTERPOLYMER TYPE A (ALLYL SUCROSE CROSSLINKED) 1.18 mL/236 mL; WATER 63.956 mL/236 mL; ALOE VERA LEAF 0.236 mL/236 mL; AMINOMETHYLPROPANOL 0.708 mL/236 mL

B.C., Hand Sanitizer, Gel, 70% Alcohol, 236mL

Active Ingredient(s)

Ethanol 70% v/v. Purpose: Antiseptic

Purpose

Antiseptic, Hand Sanitizer

Use

Hand Sanitizer to help reduce bacteria that potentially can cause disease. For use when soap and water are not available.

Warnings

Flammable. For external use only. Keep away from heat or flame.

Do not use

- on children less than 2 months of age
- on open skin wounds

When using this product keep out of eyes, ears, and mouth.

In case of contact with eyes, rinse eyes thoroughly with water.

Stop use and ask a doctor if irritation or rash occurs. These may be signs of a serious condition.

Keep out of reach of children. If swallowed, get medical help or contact a Poison Control Center right away.

Directions

- Place enough product on hands to cover all surfaces. Rub hands together until dry.
- Supervise children under 6 years of age when using this product to avoid swallowing.

Other information

- Store between 59-86℉ (15-30℃)
- Avoid freezing and excessive heat above 104℉ (40℃)

Inactive ingredients

Water, Olive Oil PEG-7 Esters, Acrylates/C10-30 Alkyl, Acrylate Crosspolymer, Aminomethyl Propanol, Aloe Barbadensis Leaf Extract